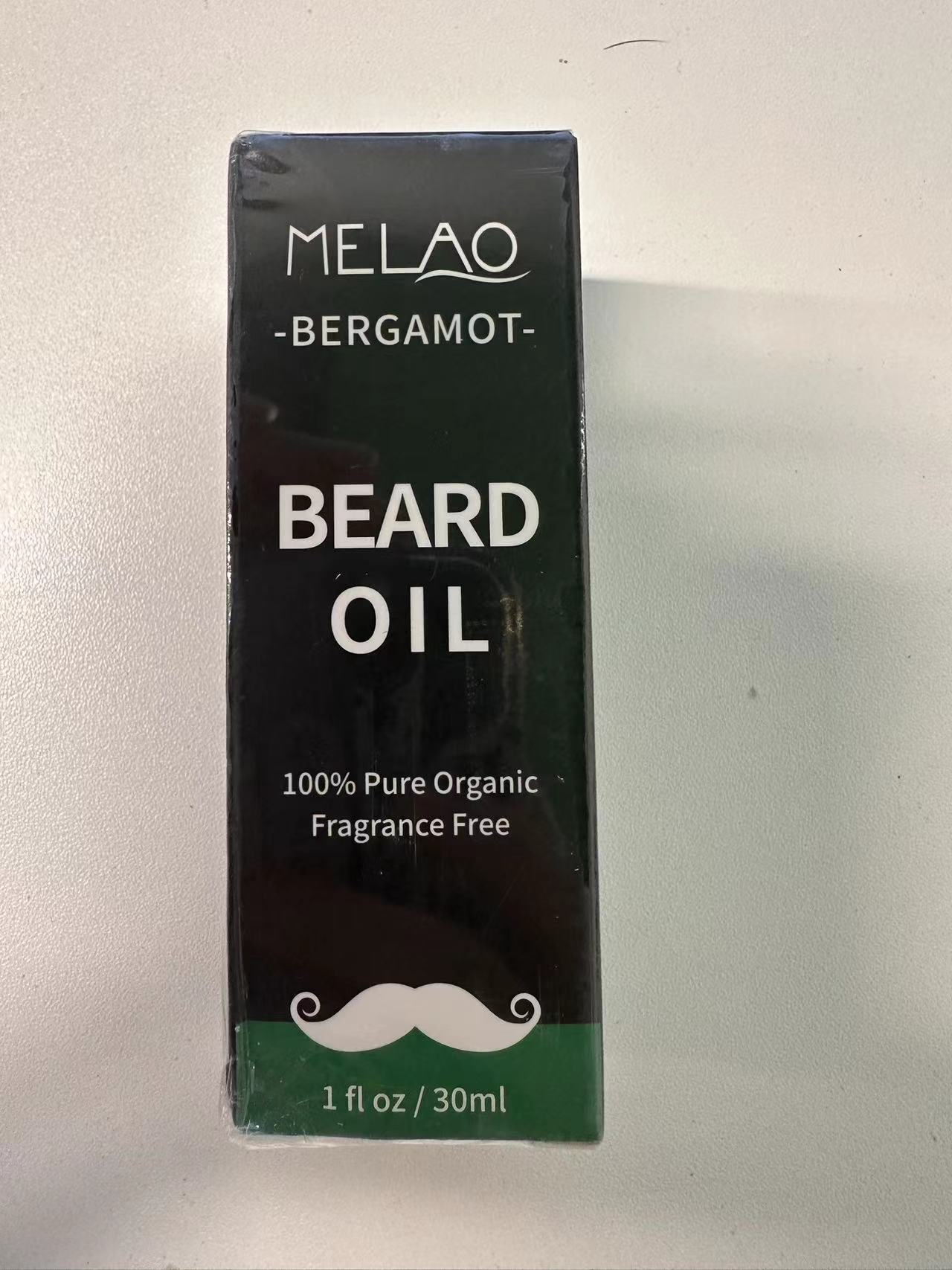 DRUG LABEL: MELAO BEARD Oil
NDC: 83566-572 | Form: LIQUID
Manufacturer: Guangzhou Yilong Cosmetics Co., Ltd
Category: otc | Type: HUMAN OTC DRUG LABEL
Date: 20240808

ACTIVE INGREDIENTS: MELISSA OFFICINALIS LEAF OIL 20 g/100 g
INACTIVE INGREDIENTS: CITRUS AURANTIUM LEAFY TWIG OIL 80 g/100 g

Active ingredients

Melissa Officinalis Leaf Oil 20%

Inactive ingredients

Citrus Aurantium Bergamia(Bergamot)Peel Oil 80%

Purpose

Protect beard hair follicles

Uses

Step 1: Clean and thoroughly dry your skin.

Step 2: Rotate the bottle cap to open the product.

Step 3: Gently apply to the surface of the skin.

Warning

For external use only.

Stop use and ask a doctor if

rash occurs

Do not use

on damaged or broken skin.

When using this product

keep out of eyes. Rinse withwater to remove.

Keep out of reach of children.

-If swallowed, get medical help or contact a Poison Control Center right away.

DOSAGE & ADMINISTRATION

Squeeze out an appropriate amount of sunscreen and spread evenly on skin.